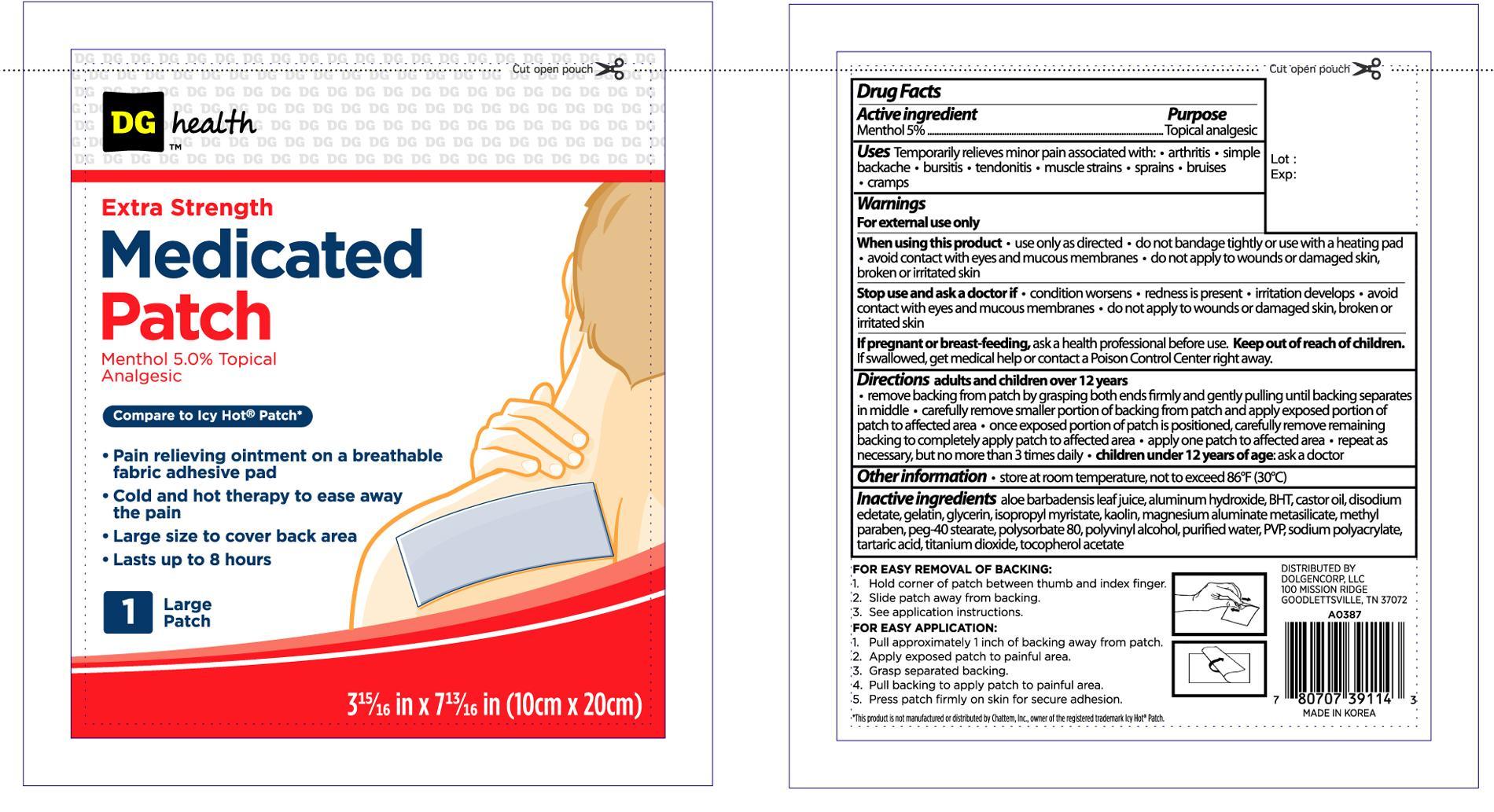 DRUG LABEL: DG HEALTH EXTRA STRENGTH MEDICATED
                
NDC: 55910-391 | Form: PATCH
Manufacturer: DOLGENCORP INC
Category: otc | Type: HUMAN OTC DRUG LABEL
Date: 20121231

ACTIVE INGREDIENTS: MENTHOL 750 mg/1 1
INACTIVE INGREDIENTS: ALUMINUM HYDROXIDE; EDETATE DISODIUM; GELATIN; KAOLIN; METHYLPARABEN; GLYCERIN; TITANIUM DIOXIDE; ISOPROPYL MYRISTATE; WATER

Drug Facts

Active ingredient Purpose

Menthol 5%...................................................................Topical analgesic

PURPOSE

Uses Temporarily relieves minor pain associated with:

- arthritis
- simple backache
- bursitis
- tendonitis
- muscle strains
- sprains
- bruises
- cramps

Warnings

For external use only

When using this product

- use only as directed
- do not bandage tightly or use with a heating pad
- avoid contact with eyes and mucous membranes
- do not apply to wounds or damaged skin, broken or irritated skin

Stop use and ask a doctor if

- conditions worsens
- redness is present
- irritation develops
- avoid contact with eyes and mucous membranes
- do not apply to wounds or damaged skin, broken or irritated skin

PREGNANCY OR BREAST FEEDING

If pregnant or breast-feeding, ask a health professional before use.

Keep out of reach of children. If swallowed, get medical help or contact a Poison Control Center right away.

INDICATIONS AND USAGE

Directions adults and children over 12 years

- remove backing from patch by grasping both ends firmly and gently pulling until backing separates in middle
- carefully remove smaller portion of backing from patch and apply exposed portion of patch to affected area
- once exposed portion of patch is positioned, carefully remove remaining backing to completely apply patch to affected area
- apply one patch to affected area
- repeat as necessary, but no more than 3 times daily
- children under 12 years of age: ask a doctor

Other information

- store at room temperature, not to exceed 86°F (30°C)

INACTIVE INGREDIENT

Inactive ingredients aloe barbadensis leaf juice, aluminum hydroxide, BHT, castor oil, disodium edetate, gelatin, glycerin, isopropyl myristate, kaolin, magnesium aluminate metasilicate, methyl paraben, peg-40 stearate, polysorbate 80, polyvinyl alcohol, purified water, PVP, sodium polyacrylate, tartaric acid, titanium dioxide, tocopherol acetate

DOSAGE AND ADMINISTRATION

DISTRIBUTED BY

DOLGEN CORP, LLC

100 MISSION RIDGE

GOODLETTSVILLE, TN 37072

MADE IN KOREA